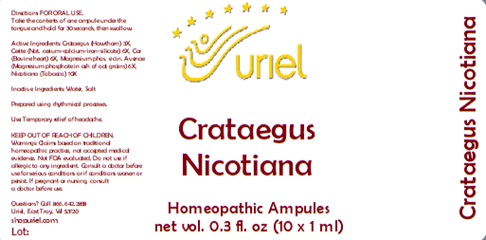 DRUG LABEL: Crataegus Nicotiana
NDC: 48951-3134 | Form: LIQUID
Manufacturer: Uriel Pharmacy Inc.
Category: homeopathic | Type: HUMAN OTC DRUG LABEL
Date: 20241120

ACTIVE INGREDIENTS: HAWTHORN LEAF WITH FLOWER 3 [hp_X]/1 mL; CERIUM 6 [hp_X]/1 mL; BEEF HEART 6 [hp_X]/1 mL; MAGNESIUM PHOSPHATE, TRIBASIC, PENTAHYDRATE 6 [hp_X]/1 mL; TOBACCO LEAF 10 [hp_X]/1 mL
INACTIVE INGREDIENTS: WATER; SODIUM CHLORIDE

Crataegus Nicotiana

INDICATIONS AND USAGE

Directions: FOR ORAL USE.

DOSAGE AND ADMINISTRATION

Take the contents of one ampule under the tongue and hold for 30 seconds, then swallow.

ACTIVE INGREDIENT

Active Ingredients: Crataegus e fol. et fruct. 3X, Cerite 6X, Cor 6X, Magnesium phos. e cin. Avenae 6X, Nicotiana e fol. 10X

Inactive Ingredients: Water, Salt

Prepared using rhythmical processes.

PURPOSE

Use: Temporary relief of headache.

KEEP OUT OF REACH OF CHILDREN.

WARNINGS

Warnings: Claims based on traditional homeopathic practice, not accepted medical evidence. Not FDA evaluated. Do not use if allergic to any ingredient. Consult a doctor before use for serious conditions or if conditions worsen or persist. If pregnant or nursing, consult
a doctor before use.

QUESTIONS

Questions? Call 866.642.2858 Uriel, East Troy, WI 53120 shopuriel.com Lot: